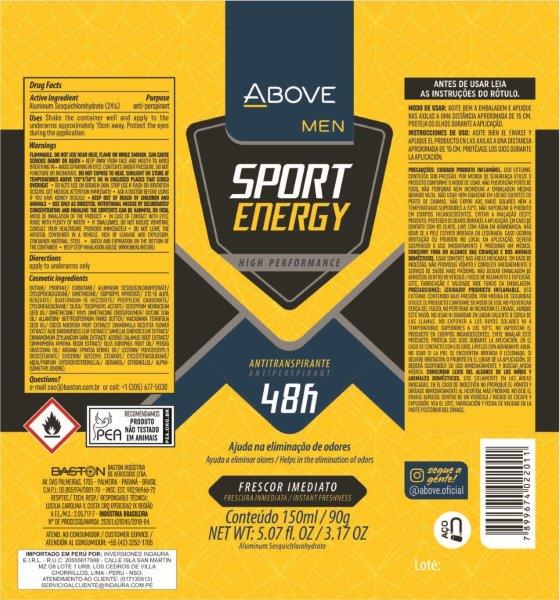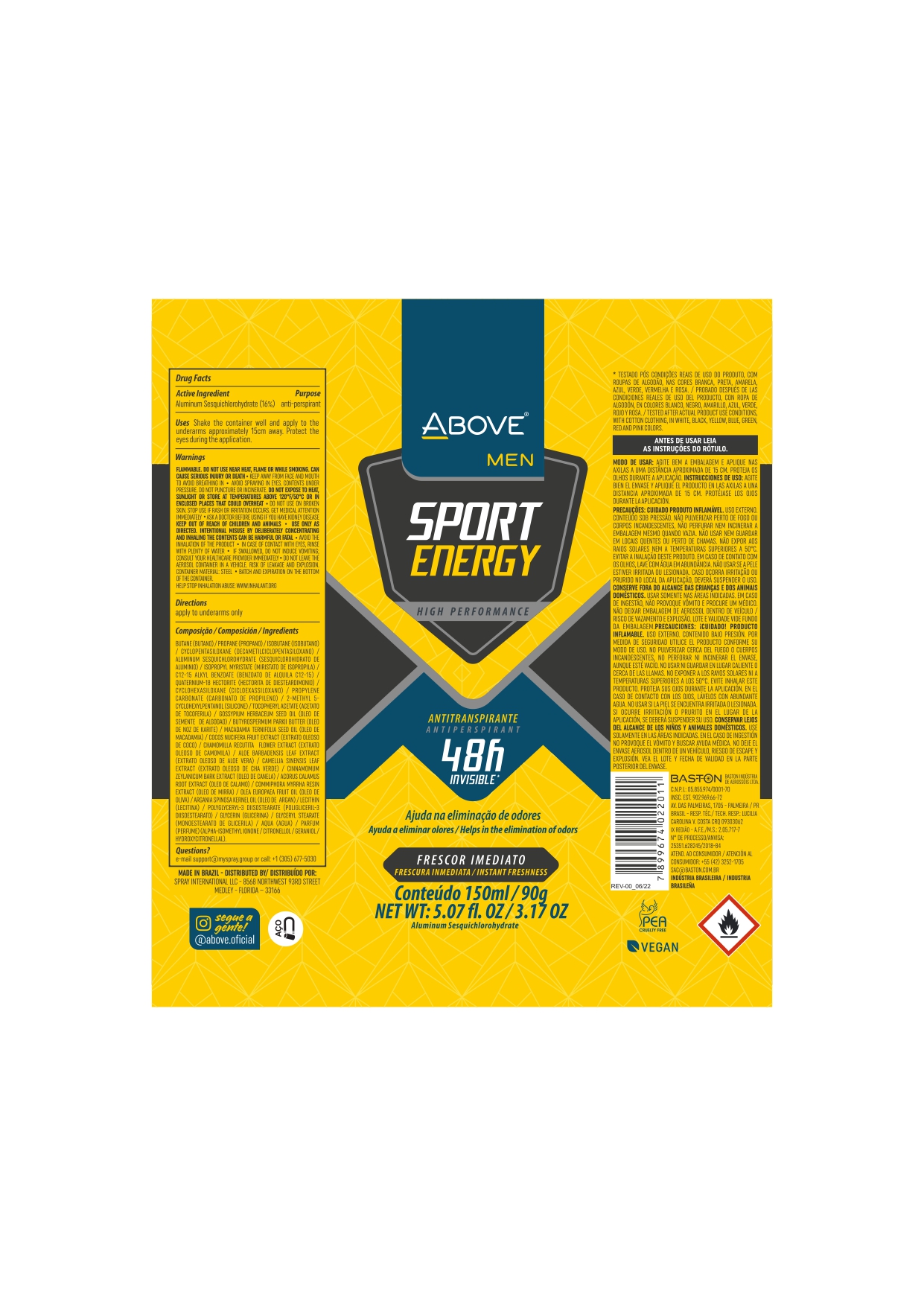 DRUG LABEL: Antiperspirant Above Sport Energy Men
NDC: 73306-1113 | Form: AEROSOL, SPRAY
Manufacturer: Baston Industria de Aerossóis Ltda
Category: otc | Type: HUMAN OTC DRUG LABEL
Date: 20241009

ACTIVE INGREDIENTS: ALUMINUM SESQUICHLOROHYDRATE 24 g/100 g
INACTIVE INGREDIENTS: VINYL DIMETHICONE/METHICONE SILSESQUIOXANE CROSSPOLYMER; GLYCERIN; PROPANE; .ALPHA.-TOCOPHEROL ACETATE; DISTEARDIMONIUM HECTORITE; POLYGLYCERYL-3 DIISOSTEARATE; LEVANT COTTON SEED; SILICA DIMETHYL SILYLATE; ACORUS CALAMUS ROOT; GREEN TEA LEAF; LECITHIN, SOYBEAN; ALOE VERA LEAF; COCONUT; ALLANTOIN; BUTANE; CHAMOMILE; ISOBUTANE; ARGAN OIL; DIMETHICONE; WATER; GLYCERYL MONOSTEARATE; ISOPROPYL MYRISTATE; AVOCADO OIL; CINNAMON BARK OIL; CYCLOMETHICONE 5; MACADAMIA OIL; PROPYLENE CARBONATE; SHEA BUTTER; MYRRH OIL

Antiperspirant Above Sport Energy Men Aerosol